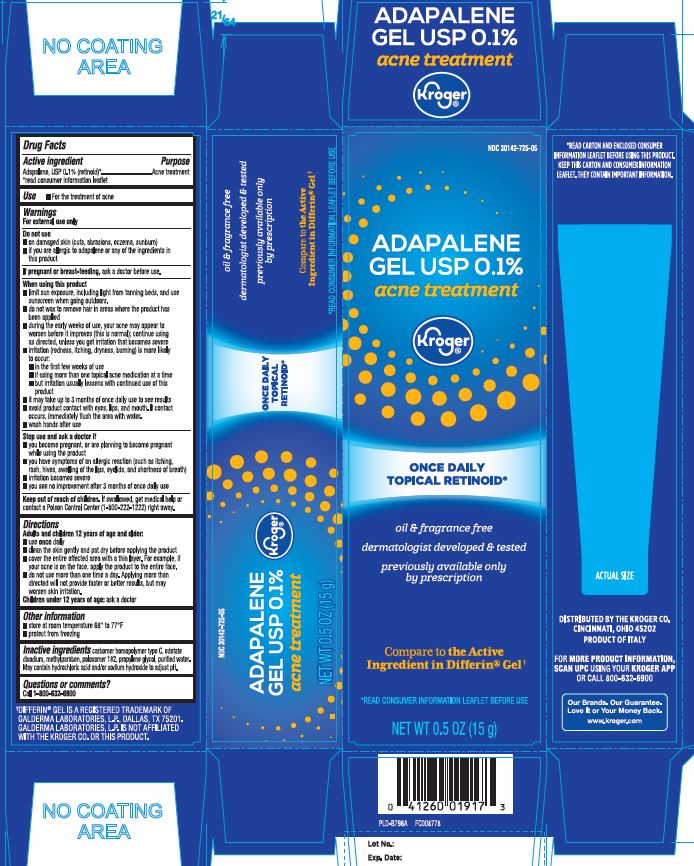 DRUG LABEL: Adapalene
NDC: 30142-725 | Form: GEL
Manufacturer: The Kroger Co.
Category: otc | Type: HUMAN OTC DRUG LABEL
Date: 20240314

ACTIVE INGREDIENTS: ADAPALENE 1 mg/1 g
INACTIVE INGREDIENTS: CARBOMER HOMOPOLYMER TYPE C (ALLYL PENTAERYTHRITOL CROSSLINKED); EDETATE DISODIUM; METHYLPARABEN; POLOXAMER 182; PROPYLENE GLYCOL; WATER; SODIUM HYDROXIDE; HYDROCHLORIC ACID

Adapalene Gel USP 0 1 percent ENE

Active ingredient

Adapalene, USP 0.1% (retinoid)*

*read consumer information leaflet

Purpose

Acne treatment

Use

- For the treatment of acne

Warnings

For external use only

Do not use

- on damaged skin (cuts, abrasions eczema, sunburn)
- if you are allergic to adapalene or any of the ingredients in this product

If pregnant or breast-feeding,

ask a doctor before use.

When using this product

- limit sun exposure, including light from tanning beds, and use sunscreen when going outdoors.
- do not wax to remove hair in areas where the product has been applied
- during the early weeks of use, your acne may appear to worsen before it improves (this is normal); continue using as directed, unless you get irritation that become severe
- irritation (redness, itching, dryness, burning) is more likely to occur:
  - in the first few weeks of use
  - if using more than one topical acne medication at a time
  - but irritation usually lessens with continued use of this product
- it may take up to 3 months of once daily use to see results
- avoid product contact eyes, lips, and mouth. If contact occurs, immediately flush the area with water.
- wash hands after use

Stop use and ask a doctor if

- you become pregnant, or planning to become pregnant while using the product
- you have symptoms of an allergic reaction (such as itching, rash, hives, swelling of the lips, eyelids, and shortness of breath)
- irritation become severe
- you see no improvement after 3 months of once daily use

Keep out of reach of children.

If swallowed, get medical help or contact a Poison Control Center (1-800-222-1222) right away.

Directions

Adults and children 12 years of age and older:

- use once daily
- clean the skin gently and pat dry before applying the product
- cover the entire affected area with a thin layer. For example, if your acne in on the face, apply the product to the entire face.
- do not use more than one time a day. Applying more than directed will not provide faster or better results, but may worsen skin irritation.
- Children under 12 years of age: ask a doctor

Other information

- store at rooms temperature 68º to 77ºF
- protect from freezing

Inactive ingredients

carbomer homopolymer type C, edetate disodium, methylparabem, poloxamer 182, propylene glycol, purified water.

May contain hydrochloric acid and/or sodium hydroxide to adjust pH.

Questions or comments?

Call 1-800-632-6900

Principal Display Panel

Compare to the Active Ingredient in Differin® Gel†

ADAPALENE GEL USP 0.1%

acne treatment

ONCE DAILY TOPICAL RETINOID*

Oil & fragrance free

dermatologist developed & tested

previously available only by prescription

*READ CONSUMER INFORMATION LEAFLET BEFORE USE

NET WT OZ (g)

*READ CARTON AND ENCLOSED CONSUMER INFORMATION LEAFLET BEFORE USING THIS PRODUCT.

KEEP THIS CARTON AND CONSUMER INFORMATION LEAFLET. THEY CONTAIN IMPORTANT INFORMATION.

†DIFFERIN® GEL IS A REGISTERED TRADEMARK OF GALDERMA LABORATORIES, L.P., DALLAS, TX 75201.

GALDERMA LABORATORIES, L.P. IS NOT AFFILIATED WITH THE KROGER CO. OR THIS PRODUCT.

DISTRIBUTED BY THE KROGER CO.

CINCINNATI, OHIO 45202

Product Label

Adapalene Gel USP 0.1%